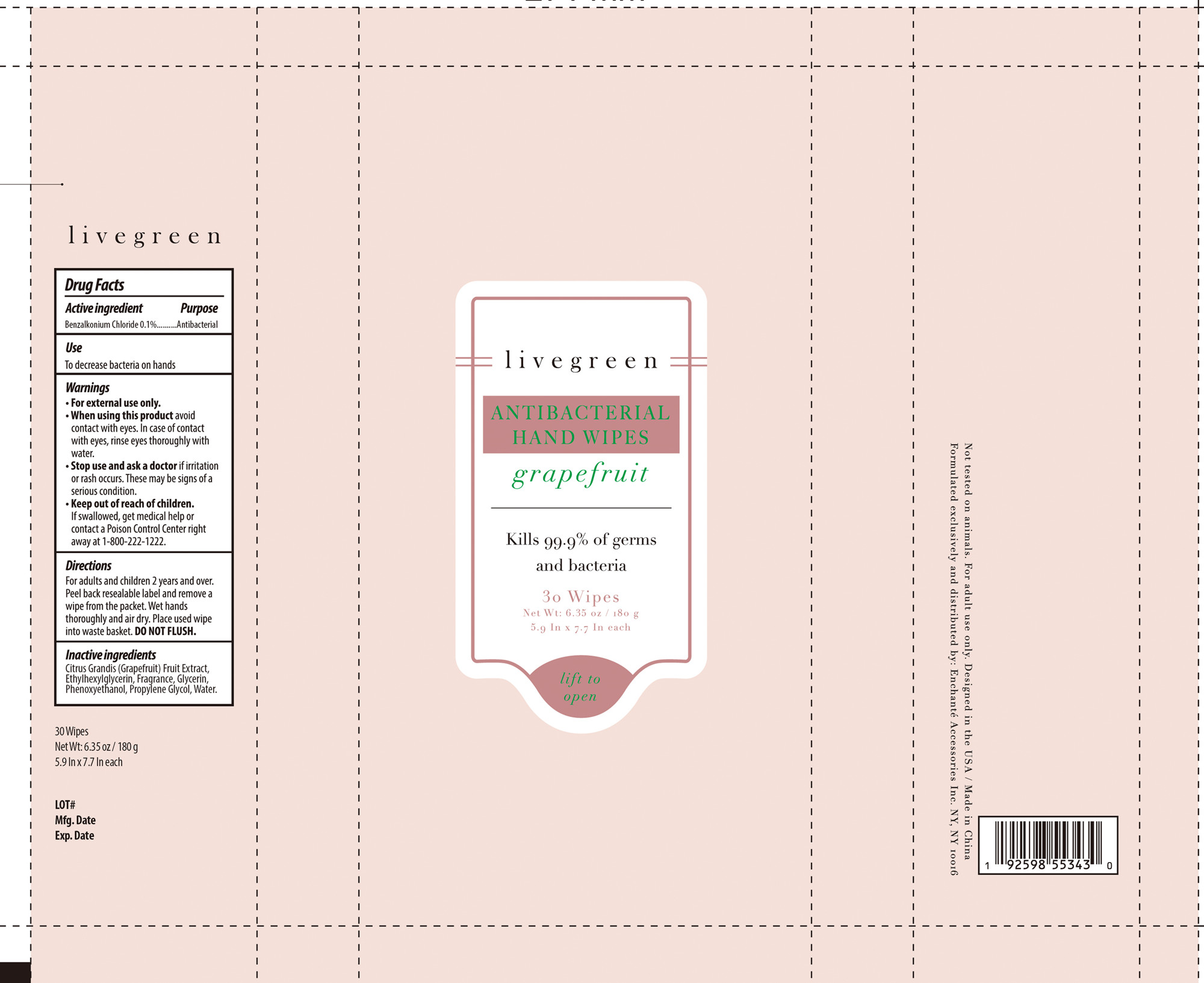 DRUG LABEL: livegreen grapefruit ANTIBACTERIAL HAND WIPES
NDC: 50563-371 | Form: SOLUTION
Manufacturer: ENCHANTE ACCESSORIES INC.
Category: otc | Type: HUMAN OTC DRUG LABEL
Date: 20201028

ACTIVE INGREDIENTS: BENZALKONIUM CHLORIDE 4.5 mg/1 1
INACTIVE INGREDIENTS: GLYCERIN; ETHYLHEXYLGLYCERIN; PHENOXYETHANOL; PROPYLENE GLYCOL; WATER; GRAPEFRUIT JUICE

50563-371_HGKTHS08

Active Ingredient

Benzalkonium Chloride 0.1%

Purpose

Antibacterial

Use

■ To decrease bacteria on hands

WARNINGS

For external use only

When using this product, avoid contact with eyes. In case of contact with eyes, rinse eyes thoroughly with water

Stop use and ask a doctor if irritation or rash occurs. These may be signs of a serious condition.

Keep out of reach of children. If swallowed, get medical help or contact a Poison Control Center right away at 1-800-222-1222

Directions

For adults and children two years and over

Peel over reusable label and remove a wipe from the packet.

Wet hands thoroughly and air dry.

Place used wipes in to waste basket. Do not flush.

Inactive ingredients

Citrus Grandis (Grapefruit) Fruit Extract, Ethylhexylglycerin, Fragrance, Glycerin, Phenoxyethanol, Propylene Glycol, Water